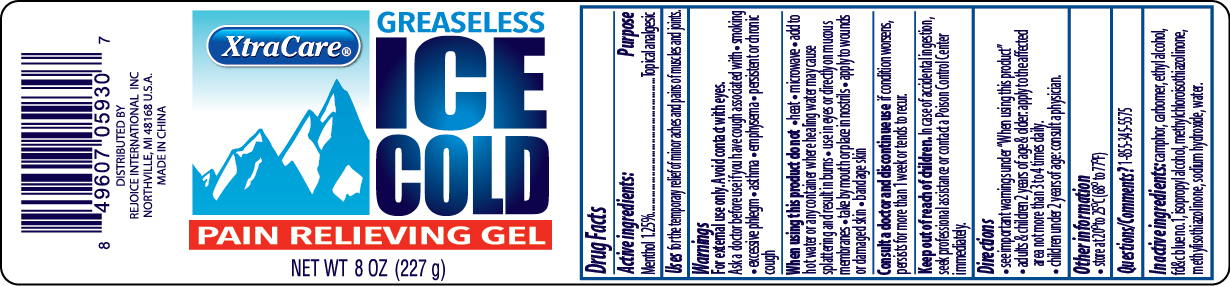 DRUG LABEL: XtraCare Ice Cold Topical Analgesic Gel
NDC: 57337-052 | Form: GEL
Manufacturer: Rejoice International
Category: otc | Type: HUMAN OTC DRUG LABEL
Date: 20231024

ACTIVE INGREDIENTS: MENTHOL 3 g/227 g
INACTIVE INGREDIENTS: CAMPHOR (NATURAL); CARBOMER COPOLYMER TYPE A (ALLYL PENTAERYTHRITOL CROSSLINKED); ALCOHOL; FD&C BLUE NO. 1; ISOPROPYL ALCOHOL; METHYLCHLOROISOTHIAZOLINONE; METHYLISOTHIAZOLINONE; SODIUM HYDROXIDE; WATER

Active Ingredients: Purpose

Menthol 1.25% ........................... Topical Analgesic

Uses

for the temporary relief of minor aches and pains of muscles and joints.

Keep out of reach of children. In case of accidental ingestion, seek professional assistance or contact a Poison Control Center immediately.

INDICATIONS AND USAGE

XtraCare® Ice Cold Topical Analgesic Gel

Net Wt 8 oz (227 g)

Warnings

For external use only. Avoid contact with eyes.

Ask a doctor before use if you have cough associated with

- smoking
- excessive phlegm
- asthma
- emphysema
- persistent or chronic cough

When using this product do not

- heat
- microwave
- add to hot water or any container where heating water may cause splattering and result in burns
- use in eyes or directly on mucous membranes
- take by mouth or place in nostrils
- apply to wounds or damaged skin
- bandage skin

Consult a doctor and discontinue use if condition worsens, persists for more than 1 week or tends to recur.

Directions

- see important warnings under "When using this product"
- adults & children 2 years of age & older: apply to the affected area not more than 3 to 4 times daily.
- children under 2 years of age: consult a physician

Inactive Ingredients:

camphor, carbomer, ethyl alcohol, FD&C blue no.1, isopropyl alcohol, methylchloroisothiazolinone, methylisothiazolinone, sodium hydroxide, water.

Other information: store at 20o to 25oC (68o to 77oF)

Questions/Comments? 1-855-345-5575

DISTRIBUTED BY:

REJOICE INTERNATIONAL INC

NORTHVILLE, MI 48168 USA

MADE IN CHINA